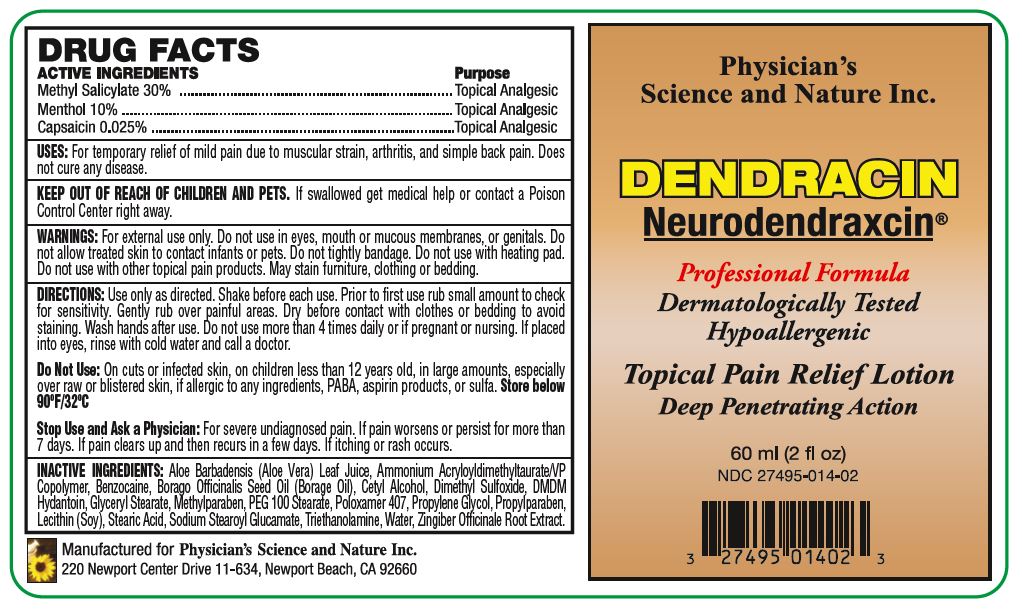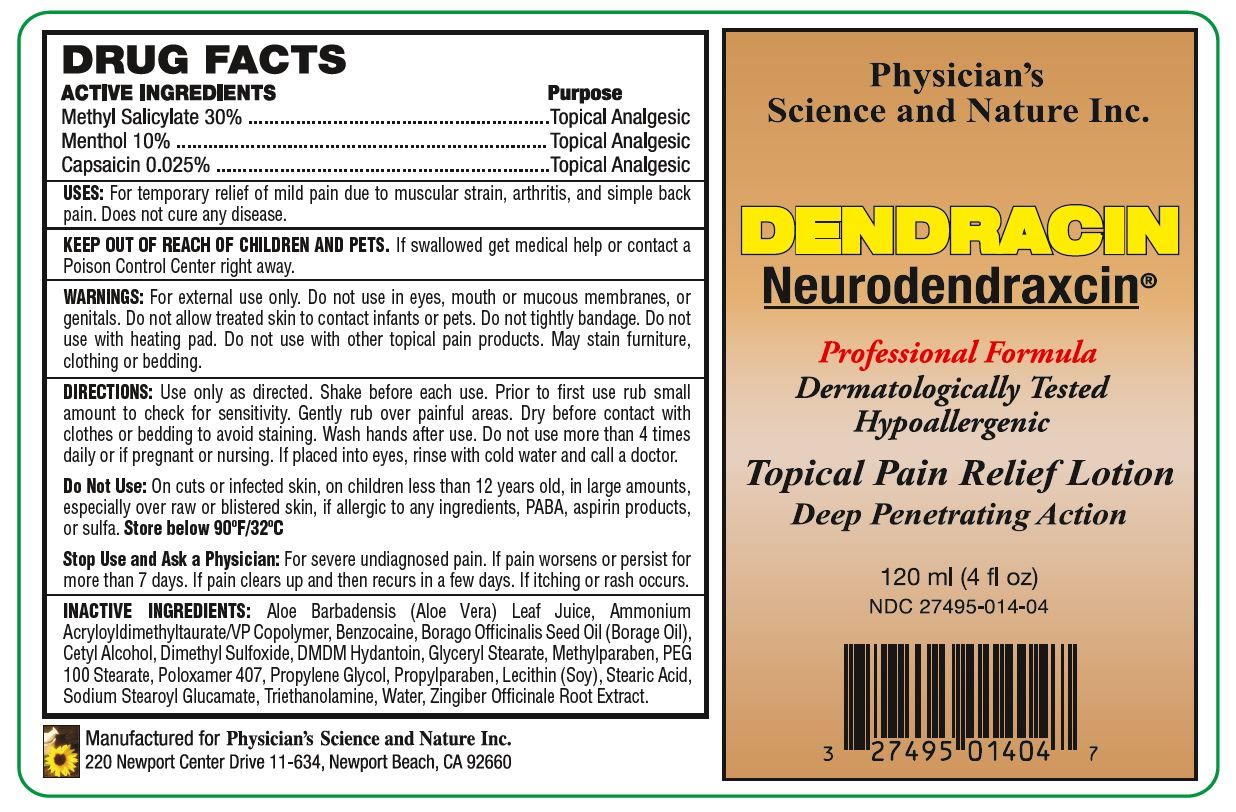 DRUG LABEL: Dendracin Neurodendraxcin
NDC: 27495-014 | Form: LOTION
Manufacturer: Physicians Science & Nature Inc.
Category: otc | Type: HUMAN OTC DRUG LABEL
Date: 20251110

ACTIVE INGREDIENTS: METHYL SALICYLATE 18 g/60 mL; MENTHOL 6 g/60 mL; CAPSAICIN 0.015 g/60 mL
INACTIVE INGREDIENTS: WATER; BENZOCAINE; GLYCERYL MONOSTEARATE; PEG-100 STEARATE; STEARIC ACID; PROPYLENE GLYCOL; CETYL ALCOHOL; DIMETHYL SULFOXIDE; POLOXAMER 407; ALOE VERA LEAF; BORAGE SEED OIL; AMMONIO METHACRYLATE COPOLYMER TYPE A; GINGER; LECITHIN, SOYBEAN; METHYLPARABEN; PROPYLPARABEN; DMDM HYDANTOIN; SODIUM STEAROYL GLUTAMATE; TROLAMINE

Dendracin Neurodendraxcin®, Topical Pain Relief Lotion

ACTIVE INGREDIENTS

Methyl Salicylate 30%
Menthol 10%
Capsaicin 0.025%

Purpose

Topical Analgesic

USES:

For temporary relief of mild pain due to muscular strain, arthritis, and simple back pain. Does not cure any disease.

Keep away from children and pets.

If swallowed get medical help or contact a Poison Control Center right away.

WARNINGS:

For external use only. Do not use in eyes, mouth, on mucous membranes, or genitals. Do not allow treated skin to contact infants or pets. Do not tightly bandage. Do not use with heating pad. Do not use with other topical pain products. May stain furniture, clothing or bedding.

DIRECTIONS:

Use only as directed. Shake before each use. Prior to first use, rub small amount to check for sensitivity. Gently rub over painful areas. Dry before contact with clothes or bedding to avoid staining. Wash hands after use. Do not use more than 4 times daily or if pregnant or nursing. If placed into eyes, rinse with cold water and call a doctor.

Do Not Use:

On cuts or infected skin, on children less than 12 years old, in large amounts, especially over raw or blistered skin, if allergic to any ingredients, PABA, aspirin products, or sulfa. Store below 90°F/32°C.

Stop Use and Ask a Physician:

For severe undiagnosed pain. If pain worsens or persist for more than 7 days. If pain clears up and then recurs in a few days. If itching or rash occurs.

INACTIVE INGREDIENTS:

Aloe Barbadensis (Aloe Vera) Leaf Juice, Ammonium Acryloyldimethyltaurate/VP Copolymer, Benzocaine, Borago Officinalis Seed Oil (Borage Oil), Cetyl Alcohol, Dimethyl Sulfoxide, DMDM Hydantoin, Glyceryl Stearate, Methylparaben, PEG 100 Stearate, Poloxamer 407, Propylene Glycol, Propylparaben, Lecithin (Soy), Stearic Acid, Sodium Stearoyl Glucamate, Triethanolamine, Water, Officinale Root Extract.

Manufactured for Physician’s Science and Nature Inc.
220 Newport Center Drive 11-634, Newport Beach, CA 92660

Principal Display Panel

Physician's Science and Nature Inc.

DENDRACIN
Neurodendraxcin®

Professional Formula
Dermatologically Tested
Hypoallergenic

Topical Pain Relief Lotion
Deep Penetrating Action

60 ml (2 fl oz)
NDC 27495-014-02

120 ml (4 fl oz)

NDC 27495-014-04